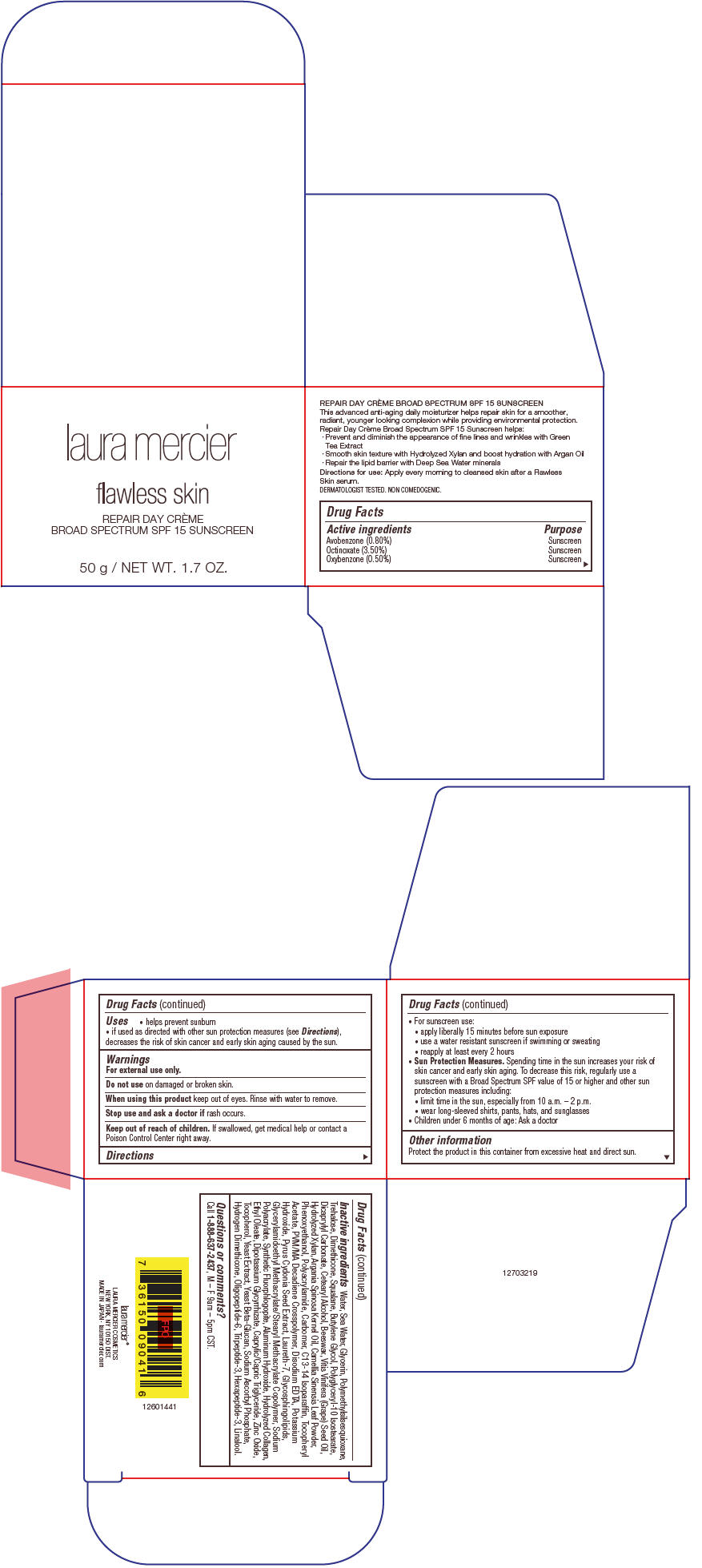 DRUG LABEL: Laura Mercier Flawless Skin Repair
NDC: 82761-056 | Form: CREAM
Manufacturer: Laura Mercier US Buyer LLC
Category: otc | Type: HUMAN OTC DRUG LABEL
Date: 20231004

ACTIVE INGREDIENTS: AVOBENZONE 8 mg/1 g; OCTINOXATE 35 mg/1 g; OXYBENZONE 5 mg/1 g
INACTIVE INGREDIENTS: WATER; SODIUM CHLORIDE; GLYCERIN; POLYMETHYLSILSESQUIOXANE (4.5 MICRONS); TREHALOSE; DIMETHICONE; SQUALANE; BUTYLENE GLYCOL; DICAPRYLYL CARBONATE; YELLOW WAX; GRAPE SEED OIL; ARGAN OIL; GREEN TEA LEAF; PHENOXYETHANOL; POLYACRYLAMIDE (1500 MW); C13-14 ISOPARAFFIN; .ALPHA.-TOCOPHEROL ACETATE; EDETATE DISODIUM; POTASSIUM HYDROXIDE; CYDONIA OBLONGA SEED; LAURETH-7; CARBOXYPOLYMETHYLENE; ARGININE; SODIUM POLYACRYLATE (2500000 MW); ALUMINUM HYDROXIDE; ETHYL OLEATE; GLYCYRRHIZINATE DIPOTASSIUM; ZINC OXIDE; TOCOPHEROL; YEAST, UNSPECIFIED; SODIUM ASCORBYL PHOSPHATE; HYDROGEN DIMETHICONE (13 CST); ACETYL HEXAPEPTIDE-8; LINALOOL, (+/-)-

Laura Mercier Flawless Skin Repair
Day Crème Broad Spectrum SPF 15 Sunscreen

Drug Facts

ACTIVE INGREDIENT

Active ingredients | Purpose
Avobenzone (0.80%) | Sunscreen
Octinoxate (3.50%) | Sunscreen
Oxybenzone (0.50%) | Sunscreen

Uses

- helps prevent sunburn
- if used as directed with other sun protection measures (see Directions), decreases the risk of skin cancer and early skin aging caused by the sun.

Warnings

For external use only.

Do not use on damaged or broken skin.

When using this product keep out of eyes. Rinse with water to remove.

Stop use and ask a doctor if rash occurs.

Keep out of reach of children. If swallowed, get medical help or contact a Poison Control Center right away.

Directions

- For sunscreen use:
  - apply liberally 15 minutes before sun exposure
  - use a water resistant sunscreen if swimming or sweating
  - reapply at least every 2 hours
- Sun Protection Measures. Spending time in the sun increases your risk of skin cancer and early skin aging. To decrease this risk, regularly use a sunscreen with a Broad Spectrum SPF value of 15 or higher and other sun protection measures including:
  - limit time in the sun, especially from 10 a.m. – 2 p.m.
  - wear long-sleeved shirts, pants, hats, and sunglasses
- Children under 6 months of age: Ask a doctor

Other information

Protect the product in this container from excessive heat and direct sun.

Inactive ingredients

Water, Sea Water, Glycerin, Polymethylsilsesquioxane, Trehalose, Dimethicone, Squalane, Butylene Glycol, Polyglyceryl-10 Isostearate, Dicaprylyl Carbonate, Cetearyl Alcohol, Beeswax, Vitis Vinifera (Grape) Seed Oil, Hydrolyzed Xylan, Argania Spinosa Kernel Oil, Camellia Sinensis Leaf Powder, Phenoxyethanol, Polyacrylamide, Carbomer, C13-14 Isoparaffin, Tocopheryl Acetate, PVM/MA Decadiene Crosspolymer, Disodium EDTA, Potassium Hydroxide, Pyrus Cydonia Seed Extract, Laureth-7, Glycosphingolipids, Glycerylamidoethyl Methacrylate/Stearyl Methacrylate Copolymer, Sodium Polyacrylate, Synthetic Fluorphlogopite, Aluminum Hydroxide, Hydrolyzed Collagen, Ethyl Oleate, Dipotassium Glycyrrhizate, Caprylic/Capric Triglyceride, Zinc Oxide, Tocopherol, Yeast Extract, Yeast Beta-Glucan, Sodium Ascorbyl Phosphate, Hydrogen Dimethicone, Oligopeptide-6, Tripeptide-3, Hexapeptide-3, Linalool.

Questions or comments?

Call 1-888-637-2437, M – F 9am – 5pm CST.

PRINCIPAL DISPLAY PANEL - 50 g Tube Carton

laura mercier

flawless skin

REPAIR DAY CRÈME
BROAD SPECTRUM SPF 15 SUNSCREEN

50 g / NET WT. 1.7 OZ.